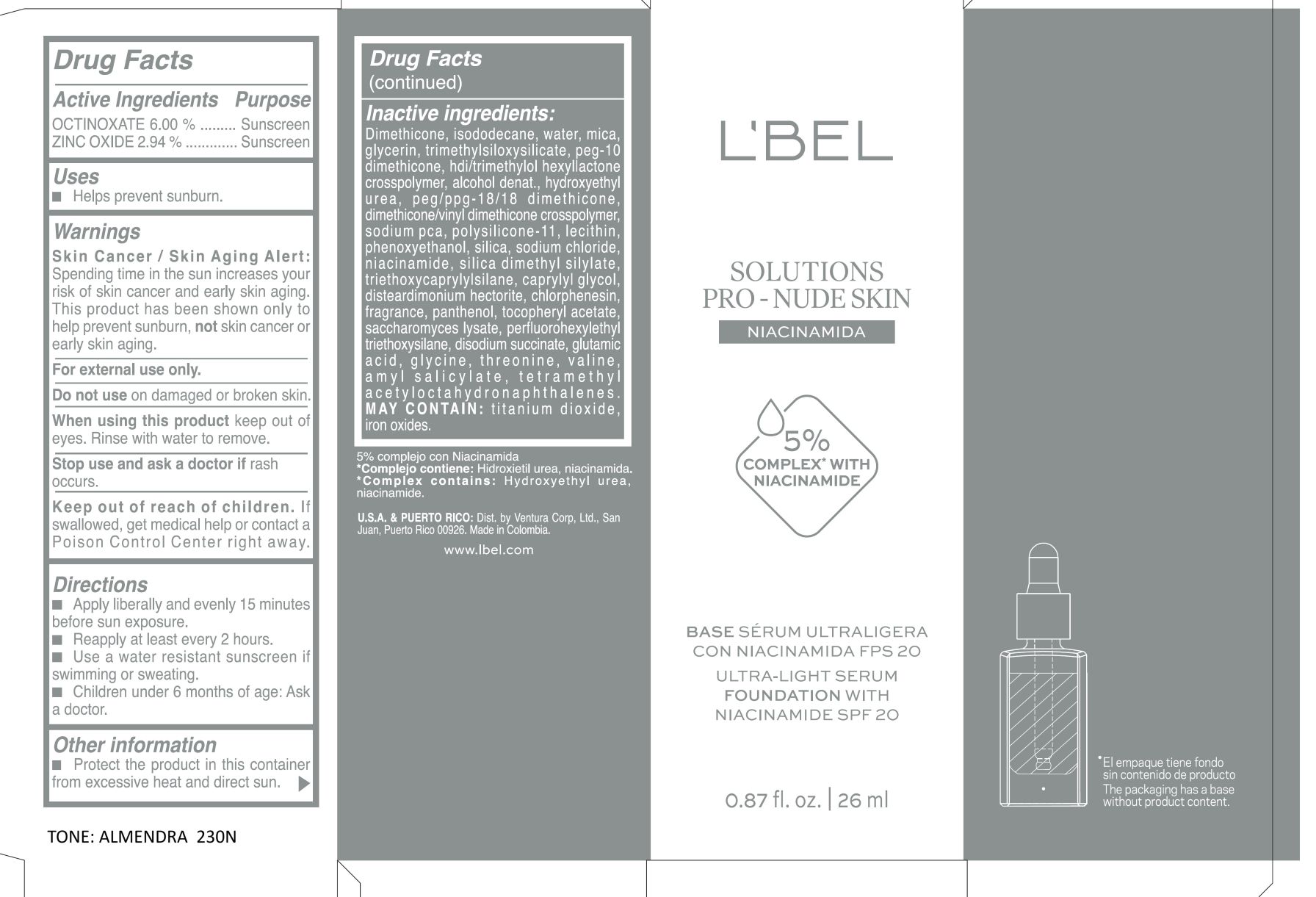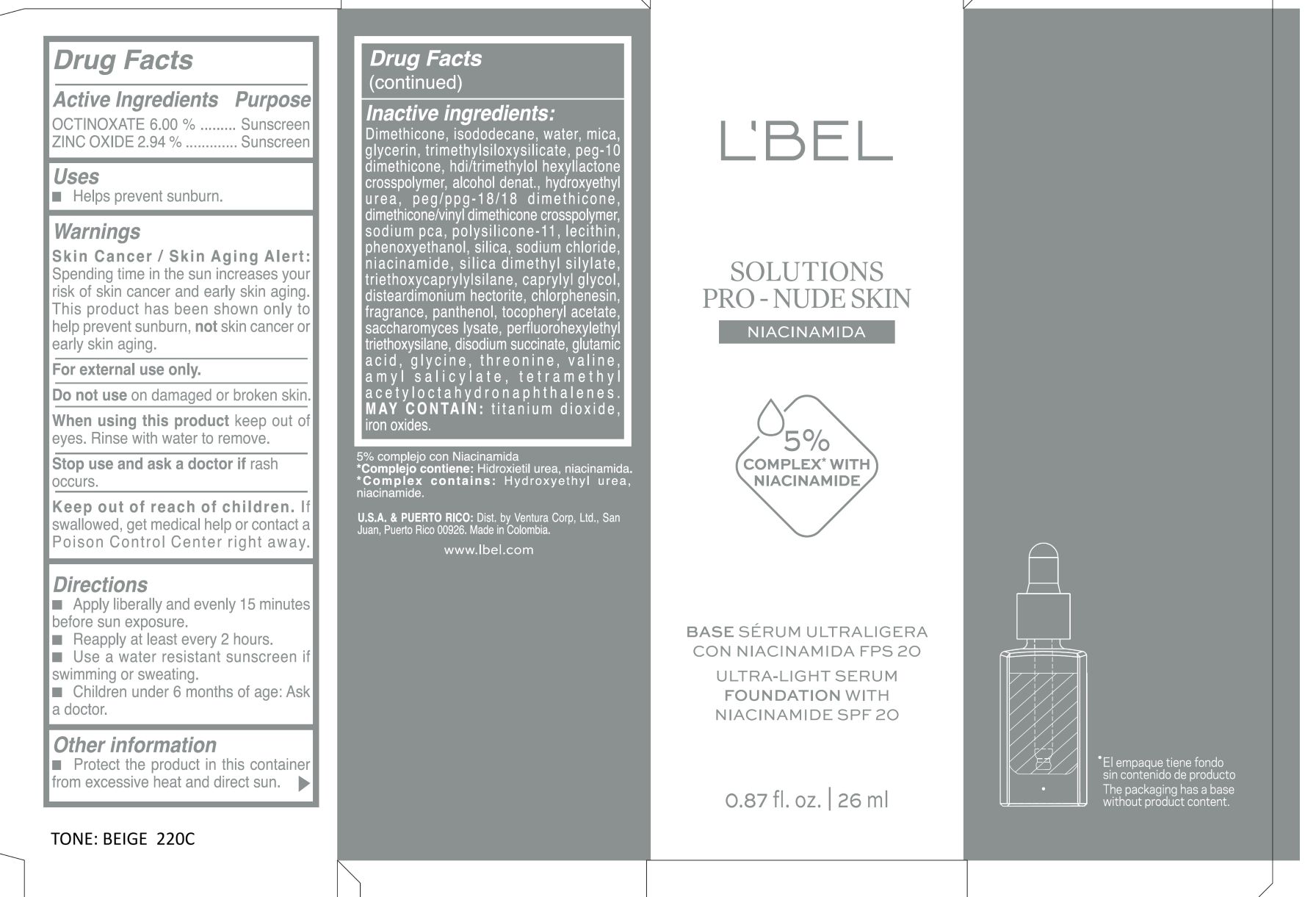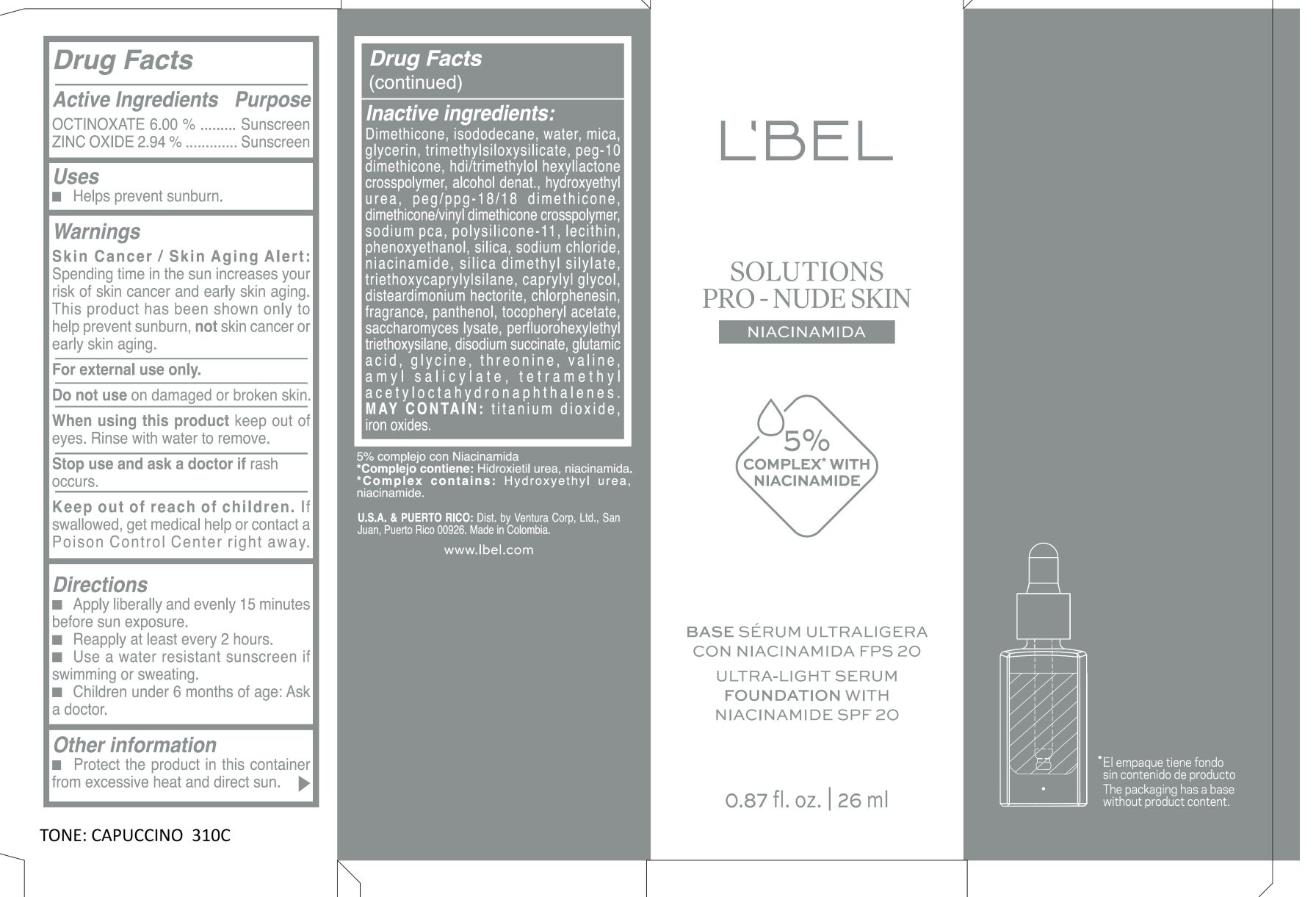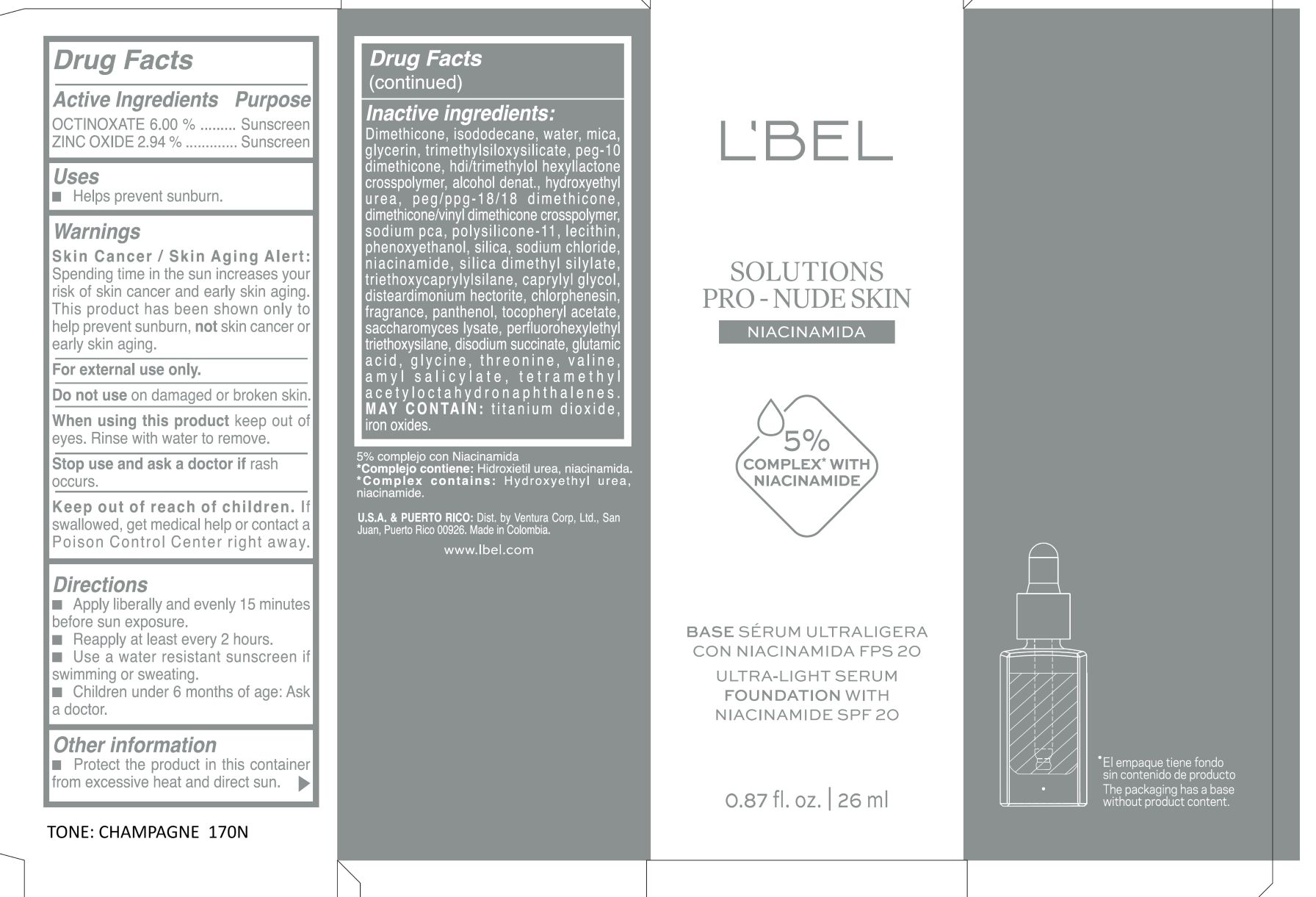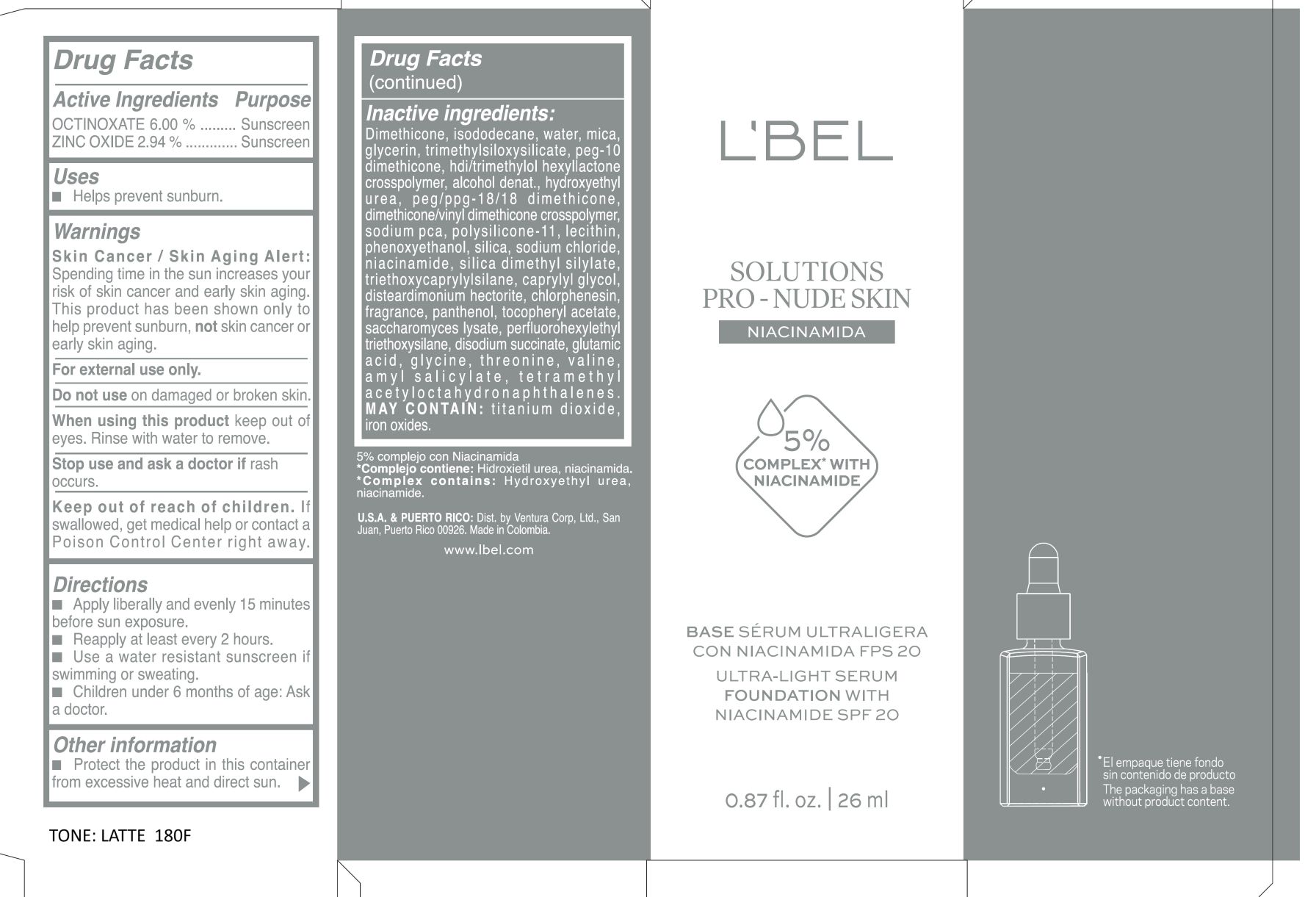 DRUG LABEL: LBEL SOLUTIONS PRO-NUDE SKIN ULTRA-LIGHT SERUM FOUNDATION WITH NIACINAMIDE SPF 20 CHAMPAGNE 170N
NDC: 14141-377 | Form: EMULSION
Manufacturer: BEL STAR S.A.
Category: otc | Type: HUMAN OTC DRUG LABEL
Date: 20250821

ACTIVE INGREDIENTS: OCTINOXATE 60 mg/1 mL; ZINC OXIDE 29.4 mg/1 mL
INACTIVE INGREDIENTS: PEG/PPG-18/18 DIMETHICONE; DISODIUM SUCCINATE; GLUTAMIC ACID; VALINE; AMYL SALICYLATE; TETRAMETHYL ACETYLOCTAHYDRONAPHTHALENES; SODIUM PCA; NIACINAMIDE; PANTHENOL; ALPHA-TOCOPHEROL ACETATE; TRIETHOXYCAPRYLYLSILANE; CAPRYLYL GLYCOL; PEG-10 DIMETHICONE (220 CST); PHENOXYETHANOL; SILICA DIMETHYL SILYLATE; DISTEARDIMONIUM HECTORITE; GLYCERIN; HDI/TRIMETHYLOL HEXYLLACTONE CROSSPOLYMER; ISODODECANE; LECITHIN, SUNFLOWER; WATER; GLYCINE; THREONINE; TITANIUM DIOXIDE; CHLORPHENESIN; SACCHAROMYCES LYSATE; FERROUS OXIDE; DIMETHICONE; MICA; SILICON DIOXIDE; SODIUM CHLORIDE; HYDROXYETHYL UREA; DIMETHICONE/VINYL DIMETHICONE CROSSPOLYMER (SOFT PARTICLE); ALCOHOL; TRIMETHYLSILOXYSILICATE (M/Q 0.6-0.8)

LBEL SOLUTIONS PRO-NUDE SKIN ULTRA-LIGHT SERUM FOUNDATION WITH NIACINAMIDE SPF 20

Active Ingredients

OCTINOXATE 6.00 %

ZINC OXIDE 2.94 %

Purpose

Sunscreen

Uses

- Helps prevent sunburn

Warnings

- Skin Cancer / Skin Aging Alert: Spending time in the sun increases your risk of skin cancer and early skin aging. This product has been shown only to help prevent sunburn, not skin cancer or early skin aging.
- For external use only.

Do not use

on damaged or broken skin.

When using this product

keep out of eyes. Rinse with water to remove.

Stop use and ask a doctor if

rash occurs.

Keep out of reach of children.

If swallowed, get medical help or contact a Poison Control Center right away.

Directions

- Apply liberally and evenly 15 minutes before sun exposure
- Reapply at least every 2 hours.
- Use a water resistant sunscreen if swimming or sweating.
- Children under 6 months of age: Ask a doctor.

Other information

- Protect the product in this container from excessive heat and direct sun.

Inactive ingredients

Dimethicone, isododecane, water, mica, glycerin, trimethylsiloxysilicate, peg-10 dimethicone, hdi/trimethylol hexyllactone crosspolymer, alcohol denat., hydroxyethyl urea, peg/ppg-18/18 dimethicone, dimethicone/vinyl dimethicone crosspolymer, sodium pca, polysilicone-11, lecithin, phenoxyethanol, silica, sodium chloride, niacinamide, silica dimethyl silylate, triethoxycaprylylsilane, caprylyl glycol, disteardimonium hectorite, chlorphenesin, fragrance, panthenol, tocopheryl acetate, saccharomyces lysate, perfluorohexylethyl triethoxysilane, disodium succinate, glutamic acid, glycine, threonine, valine, amyl salicylate, tetramethyl acetyloctahydronaphthalenes. MAY CONTAIN : titanium dioxide, iron oxides.